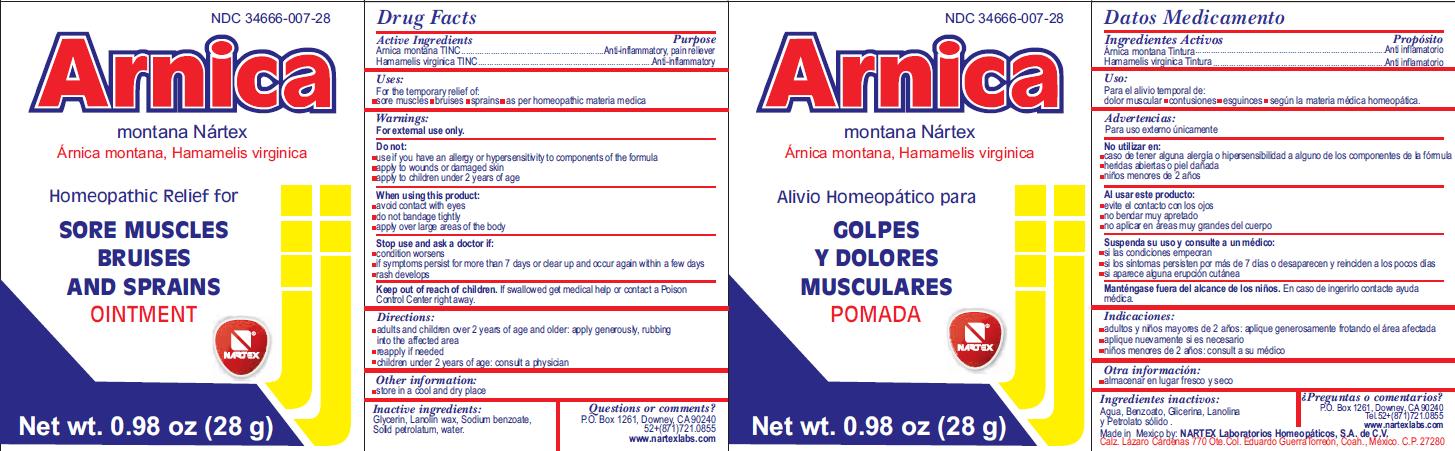 DRUG LABEL: Arnica Montana Nartex
NDC: 34666-007 | Form: OINTMENT
Manufacturer: NARTEX LABORATORIOS HOMEOPATICOS SA DE CV
Category: homeopathic | Type: HUMAN OTC DRUG LABEL
Date: 20181227

ACTIVE INGREDIENTS: ARNICA MONTANA 1.66 g/28 g; HAMAMELIS VIRGINIANA LEAF 1.66 g/28 g
INACTIVE INGREDIENTS: GLYCERIN; LANOLIN; SODIUM BENZOATE; PETROLATUM; WATER

ACTIVE INGREDIENT

Arnica Montana TINC

Hamamelis virginica TINC

PURPOSE

Anti-inflammatory, pain reliever

INDICATIONS AND USAGE

for the temporary relief of

- sore muscles
- bruises
- sprains

as per homeopathic materia medica

Warnings:

For external use only.

Do not:

- use if you have an allergy or hypersensitivity to components of the formula
- apply to wounds or damaged skin
- apply to children under 2 years of age

Stop use and ask a doctor if:

- condition worsens
- if symptoms persist for more than 7 days or clear up and occur again within a few days
- rash develops

Keep out of reach of children.

If swallowed get medical help or contact a Poison Control Center right away.

DOSAGE AND ADMINISTRATION

- adults and children over 2 years of age and older: apply generously rubbing into the affected area
- reapply if needed
- children under 2 years of age: consult a physician

INACTIVE INGREDIENT

Glycerin, Lanolin wax, Sodium benzoate, Solid petrolatum, water

Questions or comments?

P.O. Box 1261, Downey CA 90240

www.nartexlabs.com

PACKAGE LABEL

Homeopathic relief for sore muscles, bruises and sprains.